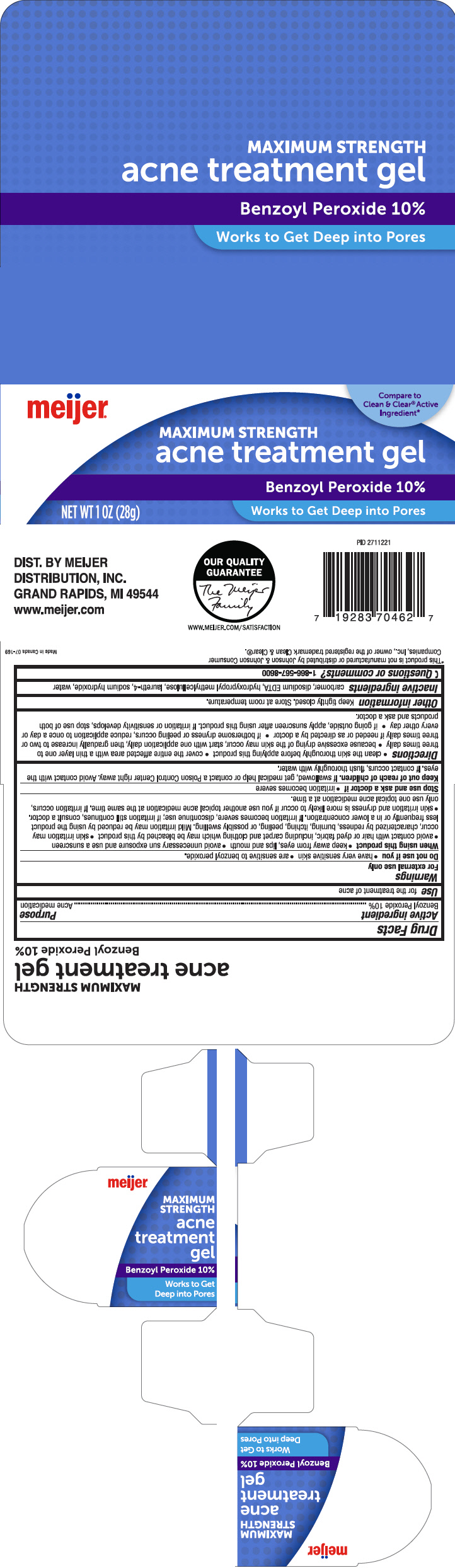 DRUG LABEL: Meijer Acne Treatment
NDC: 41250-347 | Form: GEL
Manufacturer: Meijer Distribution, Inc
Category: otc | Type: HUMAN OTC DRUG LABEL
Date: 20241106

ACTIVE INGREDIENTS: Benzoyl Peroxide 100 mg/1 g
INACTIVE INGREDIENTS: CARBOXYMETHYLCELLULOSE SODIUM, UNSPECIFIED; EDETATE DISODIUM; HYPROMELLOSE, UNSPECIFIED; Laureth-4; Sodium Hydroxide; Water

Meijer® Acne Treatment Gel
Acne medication

Drug Facts

Active ingredient

Benzoyl Peroxide 10%

Purpose

Acne medication

Use

for the treatment of acne

Warnings

For external use only

Do not use if you

- have very sensitive skin
- are sensitive to benzoyl peroxide.

When using this product

- keep away from eyes, lips and mouth
- avoid unnecessary sun exposure and use a sunscreen
- avoid contact with hair or dyed fabric, including carpet and clothing which may be bleached by this product
- skin irritation may occur, characterized by redness, burning, itching, peeling, or possibly swelling. Mild irritation may be reduced by using the product less frequently or in a lower concentration. If irritation becomes severe, discontinue use; if irritation still continues, consult a doctor.
- skin irritation and dryness is more likely to occur if you use another topical acne medication at the same time. If irritation occurs, only use one topical acne medication at a time.

Stop use and ask a doctor if

- irritation becomes severe

Keep out of reach of children. If swallowed, get medical help or contact a Poison Control Center right away. Avoid contact with the eyes. If contact occurs, flush thoroughly with water.

Directions

- Clean the skin thoroughly before applying this product
- cover the entire affected area with a thin layer one to three times daily
- because excessive drying of the skin may occur, start with one application daily, then gradually increase to two or three times daily if needed or as directed by a doctor
- if bothersome dryness or peeling occurs, reduce application to once a day or every other day
- if going outside, apply sunscreen after using this product. If irritation or sensitivity develops, stop use of both products and ask a doctor.

Other information

Keep tightly closed. Store at room temperature.

Inactive ingredients

carbomer, disodium EDTA, hydroxypropyl methylcellulose, laureth-4, sodium hydroxide, water

Questions or comments?

1-866-567-8600

DIST. BY MEIJER
DISTRIBUTION, INC.
GRAND RAPIDS, MI 49544

PRINCIPAL DISPLAY PANEL - 28 g Tube Carton

meijer®

Compare to
Clean & Clear® Active
Ingredient*

MAXIMUM STRENGTH
acne treatment gel

Benzoyl Peroxide 10%

NET WT 1 OZ (28g)

Works to Get Deep into Pores